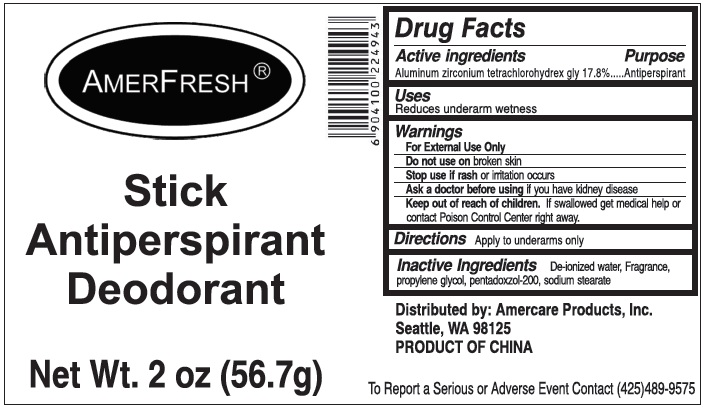 DRUG LABEL: AMERFRESH ANTIPERSPIRANT DEODORANT
NDC: 51460-4943 | Form: STICK
Manufacturer: Amercare Products, Inc
Category: otc | Type: HUMAN OTC DRUG LABEL
Date: 20181218

ACTIVE INGREDIENTS: ALUMINUM ZIRCONIUM TETRACHLOROHYDREX GLY 17.8 g/100 g
INACTIVE INGREDIENTS: WATER; PROPYLENE GLYCOL; SODIUM STEARATE

AMERFRESH STICK ANTIPERSPIRANT DEODORANT

DRUG FACTS

Active Ingredients Purpose

Aluminum Zirconium tetrachlorohydrex gly 17.8% Antiperspirant

Purpose

Antiperspirant

Uses

Reduces underarm wetness

WARNINGS

For external use only

Do not use on broken skin

Stop use if rash or irritation occurs

Ask a doctor before using if you have kidney disease

Keep out of reach of children. If swallowed, get medical help or contact Poison Control Center right away.

DOSAGE AND ADMINISTRATION

DIRECTIONS: apply to underarms only.

INACTIVE INGREDIENTS:

Deionized water, fragrance, propylene glycol, pentadoxzol-200, sodium stearate

Distributed by:

Amercare Products, Inc.

Seattle, WA 98125

PRODUCT OF CHINA

To report a serious or adverse event

Contact (425) 489-9575

PACKAGE LABEL

AMERFRESH

STICK ANTIPERSPIRANT DEODORANT

Net Wt. 2oz (56.7 g)